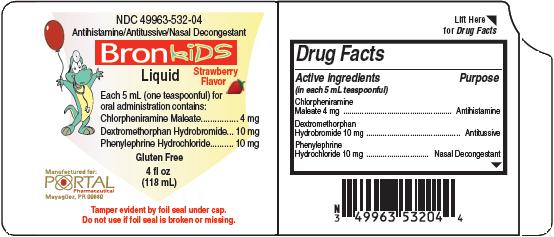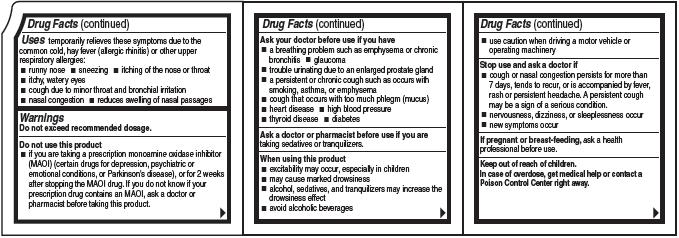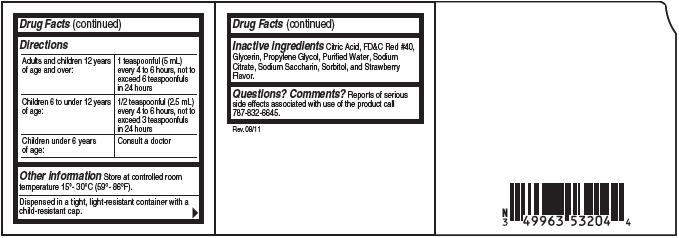 DRUG LABEL: Bronkids
NDC: 49963-532 | Form: LIQUID
Manufacturer: Portal Pharmaceutical
Category: otc | Type: HUMAN OTC DRUG LABEL
Date: 20111121

ACTIVE INGREDIENTS: Chlorpheniramine Maleate 4 mg/5 mL; Dextromethorphan Hydrobromide 10 mg/5 mL; Phenylephrine Hydrochloride 10 mg/5 mL
INACTIVE INGREDIENTS: Citric Acid; Glycerin; Propylene Glycol; Water; Sodium Citrate; Saccharin Sodium; Sorbitol

Bronkids Liquid

Drug Facts

Active ingredients
(in each 5 mL teaspoonful)
Chlorpheniramine Maleate 4 mg
Dextromethorphan Hydrobromide 10 mg
Phenylephrine Hydrochloride 10 mg

Purpose

Antihistamine
Antitussive
Nasal Decongestant

Uses

temporarily relieves these symptoms due to the common cold, hay fever (allergic rhinitis) or other upper respiratory allergies:

- runny nose
- sneezing
- itching of the nose or throat
- itchy, watery eyes
- cough due to minor throat and bronchial irritation
- nasal congestion
- reduces swelling of nasal passages

Warnings

Do not exceed recommended dosage.

Do not use this product

- if you are taking a prescription monamine oxidase inhibitor (MAOI) (certain drugs for depression, psychiatric or emotional conditions, or Parkinson's disease), or for 2 weeks after stopping the MAOI drug. If you do not know if your prescription drug contains an MAOI, ask a doctor or pharmacist before taking this product.

Ask a doctor before use if you have

- a breathing problem such as emphysema or chronic bronchitis
- glaucoma
- trouble urinating due to an enlarged prostate gland
- a persistent or chronic cough such as occurs with smoking, asthma, or emphysema
- cough that occurs with too much phlegm (mucus)
- heart disease
- high blood pressure
- thyroid disease
- diabetes

Ask a doctor or pharmacist before use if you are

taking sedatives or tranquilizers.

When using this product

- excitability may occur, especially in children
- may cause marked drowsiness
- alcohol, sedatives, and tranquilizers may increase the drowsiness effect
- avoid alcoholic beverages
- use caution when driving a motor vehicle or operating machinery

Stop use and ask a doctor if

- cough or nasal congestion persists for more than 7 days, tends to recur, or is accompanied by fever, rash or persistent headache. A persistent cough may be a sign of a serious condition
- nervousness, dizziness,or sleeplessness occur
- new symptoms occur

PREGNANCY OR BREAST FEEDING

If pregnant or breast-feeding, ask a health professional before use.

Keep out of reach of children.

In case of overdose, get medical help or contact a Poison Control Center right away.

Directions

Adults and children 12 years of age and over | 1 teaspoonful (5 mL) every 4 to 6 hours, not to exceed 6 teaspoonfuls in 24 hours
Children 6 to under 12 years of age: | 1/2 teaspoonful (2.5 mL) every 4 to 6 hours, not to exceed 3 teaspoonfuls in 24 hours
Children under 6 years of age: | Consult a doctor

Other information

Store at controlled room temperature 15°-30°C (59°-86°F).
Dispense in a tight, light-resistant container with a
child-resistant cap.

Inactive ingredients

Citric Acid, FD&C Red #40, Glycerin, Propylene Glycol, Purified Water, Sodium Citrate, Sodium Saccharin, Sorbitol, and Strawberry Flavor.

Questions? Comments?

Reports of serious side effects associated with use of the product call 787-832-6645.
Rev. 08/11

Product Packaging

The packaging below represents the labeling currently used.
Principal display panel and side panel for 118 mL label:
NDC 49963-532-04
Antihistamine/Antitussive/Nasal Decongestant
Bronkids
Liquid
Strawberry Flavor
Each 5 mL (one teaspoonful) for
oral administration contains:
Chlorpheniramine Maleate.........................4 mg
Dextromethorphan Hydrobromide.............10 mg
Phenylephrine Hydrochloride...................10 mg
Gluten Free
4 fl oz
(118 mL)
Tamper evident by foil seal under cap.
Do not use if foil seal is broken or missing.
Manufactured for:
PORTAL
Pharmaceutical
Mayaguez, PR 00680